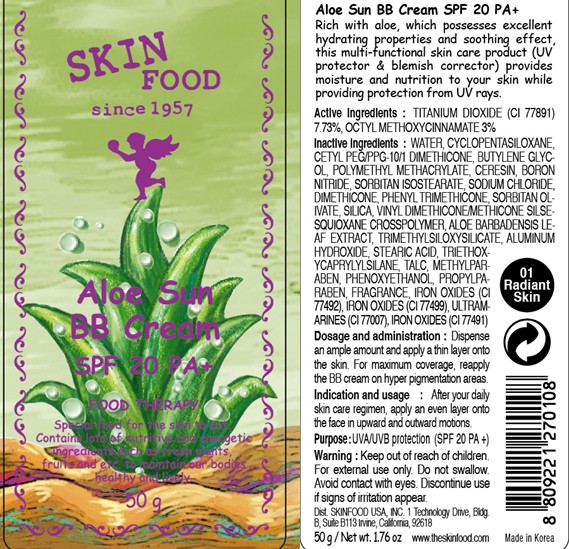 DRUG LABEL: ALOE SUN BB
NDC: 76214-027 | Form: CREAM
Manufacturer: SKINFOOD CO., LTD.
Category: otc | Type: HUMAN OTC DRUG LABEL
Date: 20110923

ACTIVE INGREDIENTS: TITANIUM DIOXIDE 3.86 g/50 g; OCTINOXATE 1.5 g/50 g
INACTIVE INGREDIENTS: WATER; CYCLOMETHICONE 5; BUTYLENE GLYCOL; CERESIN; BORON NITRIDE; SODIUM CHLORIDE; DIMETHICONE; PHENYL TRIMETHICONE; SORBITAN OLIVATE; SILICON DIOXIDE; ALUMINUM HYDROXIDE; STEARIC ACID; METHYLPARABEN; PHENOXYETHANOL; ALOE VERA LEAF; PROPYLPARABEN; TRIETHOXYCAPRYLYLSILANE; TALC

Drug Facts

Active ingredients: TITANIUM DIOXIDE 7.73%, OCTINOXATE 3%

Inactive ingredients:
WATER, CYCLOPENTASILOXANE, CETYL PEG/PPG-10/1 DIMETHICONE, BUTYLENE GLYCOL, POLYMETHYL METHACRYLATE, CERESIN, BORON NITRIDE, SORBITAN ISOSTEARATE, SODIUM CHLORIDE, DIMETHICONE, PHENYL TRIMETHICONE, SORBITAN OLIVATE, SILICA, VINYL DIMETHICONE/METHICONE SILSESQUIOXANE CROSSPOLYMER, ALOE BARBADENSIS LEAF EXTRACT, TRIMETHYLSILOXYSILICATE, ALUMINUM HYDROXIDE, STEARIC ACID, TRIETHOXYCAPRYLYLSILANE, TALC, METHYLPARABEN, PHENOXYETHANOL, PROPYLPARABEN, FRAGRANCE, IRON OXIDES (CI 77492), IRON OXIDES (CI 77499), ULTRAMARINES (CI 77007), IRON OXIDES (CI 77491)

Purpose: UVA/UVB protection (SPF20 PA+)

Warnings:
For external use only.
Avoid contact with eyes.
Discontinue use if signs of irritation appear.

Keep out of reach of children:
Keep out of reach of children.

Indication and usage:
After your daily skin care regimen, apply an even layer onto the face in upward and outward motions.

Dosage and administration:
Dispense an ample amount and apply a thin layer onto the skin.
For maximum coverage, reapply the BB cream on hyper pigmentation areas.